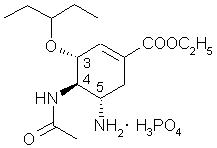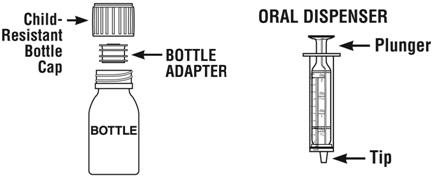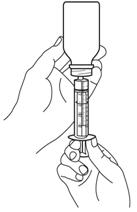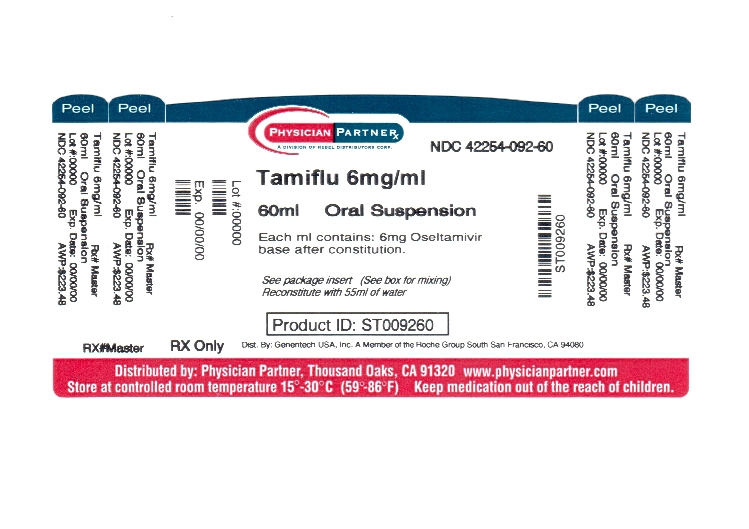 DRUG LABEL: Tamiflu
NDC: 42254-092 | Form: POWDER, FOR SUSPENSION
Manufacturer: Rebel Distributors Corp
Category: prescription | Type: HUMAN PRESCRIPTION DRUG LABEL
Date: 20111227

ACTIVE INGREDIENTS: Oseltamivir Phosphate 6 mg/1 mL
INACTIVE INGREDIENTS: sorbitol; monosodium citrate; xanthan gum; titanium dioxide; sodium benzoate; SACCHARIN SODIUM DIHYDRATE

HIGHLIGHTS OF PRESCRIBING INFORMATION

These highlights do not include all the information needed to use TAMIFLU safely and effectively. See full prescribing information for TAMIFLU.
TAMIFLU® (oseltamivir phosphate) capsules
TAMIFLU® (oseltamivir phosphate) for oral suspension
Initial U.S. Approval: 1999

RECENT MAJOR CHANGES

Dosage and Administration (2.1, 2.2, 2.3, 2.7, 2.8) | 3/2011

1 INDICATIONS AND USAGE

TAMIFLU is an influenza neuraminidase inhibitor indicated for:

- Treatment of influenza in patients 1 year and older who have been symptomatic for no more than 2 days. (1.1)
- Prophylaxis of influenza in patients 1 year and older. (1.2)

Important Limitations of Use:

- Efficacy not established in patients who begin therapy after 48 hours of symptoms. (1.3)
- Not a substitute for annual influenza vaccination. (1.3)
- No evidence of efficacy for illness from agents other than influenza viruses types A and B. (1.3)
- Consider available information on influenza drug susceptibility patterns and treatment effects when deciding whether to use. (1.3)

2 DOSAGE AND ADMINISTRATION

Treatment of influenza (2.2)

- Adults and adolescents (13 years and older): 75 mg twice daily for 5 days
- Pediatric patients (1 year and older): Based on weight twice daily for 5 days
- Renally impaired patients (creatinine clearance 10-30 mL/min): Reduce to 75 mg once daily for 5 days (2.4)

Prophylaxis of influenza (2.3)

- Adults and adolescents (13 years and older): 75 mg once daily for at least 10 days
  - -Community outbreak: 75 mg once daily for up to 6 weeks
- Pediatric patients (1 year and older): Based on weight once daily for 10 days
  - -Community outbreak: Based on weight once daily for up to 6 weeks
- Renally impaired patients (creatinine clearance 10-30 mL/min): Reduce to 75 mg once every other day or 30 mg once daily (2.4)

3 DOSAGE FORMS AND STRENGTHS

- Capsules: 30 mg, 45 mg, 75 mg (3)
- Powder for oral suspension: 360 mg oseltamivir base (constituted to a final concentration of 6 mg/mL) (3)

4 CONTRAINDICATIONS

Patients with known serious hypersensitivity to oseltamivir or any of the components of TAMIFLU (4)

5 WARNINGS AND PRECAUTIONS

- Serious skin/hypersensitivity reactions: Discontinue TAMIFLU and initiate appropriate treatment if allergic-like reactions occur or are suspected. (5.1)
- Neuropsychiatric events: Patients with influenza, including those receiving TAMIFLU, particularly pediatric patients, may be at an increased risk of confusion or abnormal behavior early in their illness. Monitor for signs of abnormal behavior. (5.2)

6 ADVERSE REACTIONS

Most common adverse reactions (>1% and more common than with placebo):

- Treatment studies – Nausea, vomiting (6.1)
- Prophylaxis studies – Nausea, vomiting, diarrhea, abdominal pain (6.1)

To report SUSPECTED ADVERSE REACTIONS, contact Genentech at 1-888-835-2555 or FDA at 1-800-FDA-1088 or www.fda.gov/medwatch

7 DRUG INTERACTIONS

Live attenuated influenza vaccine, intranasal (7):

- Do not administer until 48 hours following cessation of TAMIFLU.
- Do not administer TAMIFLU until 2 weeks following administration of the live attenuated influenza vaccine, unless medically indicated.

8 USE IN SPECIFIC POPULATIONS

- Pregnancy: No data in pregnant women. Use only if clearly needed. (8.1)
- Nursing mothers: Caution should be exercised when administered to a nursing woman. (8.3).
- Pediatric use: Safety and efficacy not established in patients less than 1 year old. (8.4)

FULL PRESCRIBING INFORMATION

1 INDICATIONS AND USAGE

1.1 Treatment of Influenza

TAMIFLU is indicated for the treatment of uncomplicated acute illness due to influenza infection in patients 1 year and older who have been symptomatic for no more than 2 days.

1.2 Prophylaxis of Influenza

TAMIFLU is indicated for the prophylaxis of influenza in patients 1 year and older.

1.3 Limitations of Use

The following points should be considered before initiating treatment or prophylaxis with TAMIFLU:

- Efficacy of TAMIFLU in patients who begin treatment after 48 hours of symptoms has not been established.
- TAMIFLU is not a substitute for early influenza vaccination on an annual basis as recommended by the Centers for Disease Control and Prevention Advisory Committee on Immunization Practices.
- There is no evidence for efficacy of TAMIFLU in any illness caused by agents other than influenza viruses types A and B.
- Influenza viruses change over time. Emergence of resistance mutations could decrease drug effectiveness. Other factors (for example, changes in viral virulence) might also diminish clinical benefit of antiviral drugs. Prescribers should consider available information on influenza drug susceptibility patterns and treatment effects when deciding whether to use TAMIFLU.

2 DOSAGE AND ADMINISTRATION

2.1 Dosing for Treatment and Prophylaxis of Influenza

TAMIFLU may be taken with or without food [see Clinical Pharmacology (12.3)]. However, when taken with food, tolerability may be enhanced in some patients.

The recommended oral treatment and prophylaxis dose of TAMIFLU for patients 1 year of age and older is shown in Table 1.

Table 1 Treatment and Prophylaxis Dosing of Oral TAMIFLU for Influenza For Patients 1 Year of Age and Older Based on Body Weight
Weight (kg) | Weight (lbs) | Treatment Dosing for 5 days | Prophylaxis Dosing for 10 days | Volume of Oral Suspension (6 mg/mL) for each Dose [A 10 mL oral dosing dispenser is provided with the oral suspension. In the event that the dispenser provided is lost or damaged, another dosing dispenser may be used to deliver the volumes.] | Number of Bottles of Oral Suspension to Dispense | Number of Capsules and Strength to Dispense
15 kg or less | 33 lbs or less | 30 mg twice daily | 30 mg once daily | 5 mL | 1 bottle | 10 Capsules 30 mg
16 kg thru 23 kg | 34 lbs thru 51 lbs | 45 mg twice daily | 45 mg once daily | 7.5 mL | 2 bottles | 10 Capsules 45 mg
24 kg thru 40 kg | 52 lbs thru 88 lbs | 60 mg twice daily | 60 mg once daily | 10 mL | 2 bottles | 20 Capsules 30 mg
41 kg or more | 89 lbs or more | 75 mg twice daily | 75 mg once daily | 12.5 mL [Delivery of this TAMIFLU for Oral Suspension dose requires administering 10 mL followed by another 2.5 mL.] | 3 bottles | 10 Capsules 75 mg

2.2 Standard Dosage – Treatment of Influenza

Adults and Adolescents

The recommended oral dose of TAMIFLU for treatment of influenza in adults and adolescents 13 years and older is 75 mg twice daily for 5 days. Treatment should begin within 2 days of onset of symptoms of influenza. TAMIFLU for oral suspension may be used by patients who cannot swallow a capsule (see Table 1).

Pediatric Patients

TAMIFLU is not indicated for treatment of influenza in pediatric patients younger than 1 year.

The recommended oral dose of TAMIFLU for pediatric patients 1 year and older is shown in Table 1. For pediatric patients who cannot swallow capsules, TAMIFLU for oral suspension is the preferred formulation. If the oral suspension product is not available, TAMIFLU capsules may be opened and mixed with sweetened liquids such as regular or sugar-free chocolate syrup, corn syrup, caramel topping, or light brown sugar (dissolved in water). If the appropriate strengths of TAMIFLU capsules are not available to mix with sweetened liquids and the oral suspension product is not available, then a pharmacist may compound an emergency supply of oral suspension from TAMIFLU 75 mg capsules [see Dosage and Administration (2.8)].

2.3 Standard Dosage – Prophylaxis of Influenza

Adults and Adolescents

The recommended oral dose of TAMIFLU for prophylaxis of influenza in adults and adolescents 13 years and older following close contact with an infected individual is 75 mg once daily for at least 10 days. Therapy should begin within 2 days of exposure. The recommended dose for prophylaxis during a community outbreak of influenza is 75 mg once daily. Safety and efficacy have been demonstrated for up to 6 weeks in immunocompetent patients. The duration of protection lasts for as long as dosing is continued. Safety has been demonstrated for up to 12 weeks in immunocompromised patients. TAMIFLU for oral suspension may also be used by patients who cannot swallow a capsule (see Table 1).

Pediatric Patients

The safety and efficacy of TAMIFLU for prophylaxis of influenza in pediatric patients younger than 1 year of age have not been established.

The recommended oral dose of TAMIFLU for pediatric patients 1 year and older following close contact with an infected individual is shown in Table 1. For pediatric patients who cannot swallow capsules, TAMIFLU for oral suspension is the preferred formulation. If the oral suspension product is not available, TAMIFLU capsules may be opened and mixed with sweetened liquids such as regular or sugar-free chocolate syrup, corn syrup, caramel topping, or light brown sugar (dissolved in water). If the appropriate strengths of TAMIFLU capsules are not available to mix with sweetened liquids and the oral suspension product is not available, then a pharmacist may compound an emergency supply of oral suspension from TAMIFLU 75 mg capsules [see Dosage and Administration (2.8)].

Prophylaxis in pediatric patients following close contact with an infected individual is recommended for 10 days. Therapy should begin within 2 days of exposure. For prophylaxis in pediatric patients during a community outbreak of influenza, dosing may be continued for up to 6 weeks.

2.4 Renal Impairment

Data are available on plasma concentrations of oseltamivir carboxylate following various dosing schedules in patients with renal impairment [see Clinical Pharmacology (12.3)].

Treatment of Influenza

Dose adjustment is recommended for adult patients with creatinine clearance between 10 and 30 mL/min receiving TAMIFLU for the treatment of influenza. In these patients it is recommended that the dose be reduced to 75 mg of TAMIFLU once daily for 5 days. No recommended dosing regimens are available for patients with end-stage renal disease undergoing routine hemodialysis or continuous peritoneal dialysis treatment.

Prophylaxis of Influenza

For the prophylaxis of influenza, dose adjustment is recommended for adult patients with creatinine clearance between 10 and 30 mL/min receiving TAMIFLU. In these patients it is recommended that the dose be reduced to 75 mg of TAMIFLU every other day or 30 mg TAMIFLU every day. No recommended dosing regimens are available for patients undergoing routine hemodialysis and continuous peritoneal dialysis treatment with end-stage renal disease.

2.5 Hepatic Impairment

No dose adjustment is recommended for patients with mild or moderate hepatic impairment (Child-Pugh score ≤9) [see Clinical Pharmacology (12.3)].

2.6 Geriatric Patients

No dose adjustment is required for geriatric patients [see Use in Specific Populations (8.5) and Clinical Pharmacology (12.3)].

2.7 Preparation of TAMIFLU for Oral Suspension

It is recommended that TAMIFLU for oral suspension be constituted by the pharmacist prior to dispensing to the patient:

- a)Tap the closed bottle several times to loosen the powder.
- b) Measure 55 mL of water in a graduated cylinder.
- c)Add the total amount of water for constitution to the bottle and shake the closed bottle well for 15 seconds.
- d)Remove the child-resistant cap and push bottle adapter into the neck of the bottle.
- e)Close bottle with child-resistant cap tightly. This will assure the proper seating of the bottle adapter in the bottle and child-resistant status of the cap.

Label the bottle with instructions to Shake Well before each use.

The constituted TAMIFLU for oral suspension (6 mg/mL) should be used within 17 days of preparation when stored under refrigeration or within 10 days if stored at controlled room temperature; the pharmacist should write the date of expiration of the constituted suspension on a pharmacy label. The patient package insert and oral dispenser should be dispensed to the patient.

2.8 Emergency Compounding of an Oral Suspension from 75 mg TAMIFLU Capsules (Final Concentration 6 mg/mL)

The following directions are provided for use only during emergency situations. These directions are not intended to be used if the FDA-approved, commercially manufactured TAMIFLU for oral suspension is readily available from wholesalers or the manufacturer.

Compounding an oral suspension with this procedure will provide one patient with enough medication for a 5-day course of treatment or a 10-day course of prophylaxis.

Commercially manufactured TAMIFLU for oral suspension (6 mg/mL) is the preferred product for pediatric and adult patients who have difficulty swallowing capsules or where lower doses are needed. In the event that TAMIFLU for oral suspension is not available, the pharmacist may compound a suspension (6 mg/mL) from TAMIFLU capsules 75 mg using one of these vehicles: Cherry Syrup (Humco®), Ora-Sweet® SF (sugar-free) (Paddock Laboratories), or simple syrup. Other vehicles have not been studied. This compounded suspension should not be used for convenience or when the FDA-approved TAMIFLU for oral suspension is commercially available.

First, calculate the total volume of an oral suspension needed to be compounded and dispensed for each patient. The total volume required is determined by the weight of the patient (see Table 2).

Table 2 Volume of an Oral Suspension (6 mg/mL) Needed to be Compounded Based Upon the Patient's Body Weight
Weight (kg) | Weight (lbs) | Total Volume to Compound per Patient (mL)
15 kg or less | 33 lbs or less | 75 mL
16 thru 23 kg | 34 thru 51 lbs | 100 mL
24 thru 40 kg | 52 thru 88 lbs | 125 mL
41 kg or more | 89 lbs or more | 150 mL

Second, determine the number of capsules and the amount of water and vehicle (Cherry Syrup, Ora-Sweet® SF, or simple syrup) that are needed to prepare the total volume (determined from Table 2: 75 mL, 100 mL, 125 mL, or 150 mL) of compounded oral suspension (6 mg/mL) (see Table 3).

Table 3 Number of TAMIFLU 75 mg Capsules and Amount of Vehicle (Cherry Syrup, Ora-Sweet® SF, or Simple Syrup) Needed to Prepare the Total Volume of a Compounded Oral Suspension (6 mg/mL)
Total Volume of Compounded Oral Suspension to be Prepared | 75 mL | 100 mL | 125 mL | 150 mL
Number of TAMIFLU 75 mg Capsules [Includes overage to ensure all doses can be delivered] | 6 capsules (450 mg oseltamivir) | 8 capsules (600 mg oseltamivir) | 10 capsules (750 mg oseltamivir) | 12 capsules (900 mg oseltamivir)
Amount of Water | 5 mL | 7 mL | 8 mL | 10 mL
Volume of Vehicle
Cherry Syrup (Humco®) OR Ora-Sweet® SF (Paddock Laboratories) OR simple syrup | 69 mL | 91 mL | 115 mL | 137 mL

Third, follow the procedure below for compounding the oral suspension (6 mg/mL) from TAMIFLU capsules 75 mg:

1. Place the specified amount of water into a polyethyleneterephthalate (PET) or glass bottle (see Table 3).
2. Carefully separate the capsule body and cap and pour the contents of the required number of TAMIFLU 75 mg capsules into the PET or glass bottle.
3. Gently swirl the suspension to ensure adequate wetting of the TAMIFLU powder for at least 2 minutes.
4. Slowly add the specified amount of vehicle to the bottle.
5. Close the bottle using a child-resistant cap and shake well for 30 seconds to completely dissolve the active drug and to ensure homogeneous distribution of the dissolved drug in the resulting suspension. (Note: The active drug, oseltamivir phosphate, readily dissolves in the specified vehicles. The suspension is caused by inert ingredients of TAMIFLU capsules which are insoluble in these vehicles.)
6. Put an ancillary label on the bottle indicating "Shake Well Before Use."
7. Instruct the parent or caregiver that any unused suspension remaining in the bottle following completion of therapy must be discarded by either affixing an ancillary label to the bottle or adding a statement to the pharmacy label instructions.
8. Place an appropriate expiration date on the label according to storage conditions below.

Storage of the Emergency Compounded Suspension

- Refrigeration: Stable for 5 weeks (35 days) when stored in a refrigerator at 2° to 8°C (36° to 46°F).
- Room Temperature: Stable for five days (5 days) when stored at room temperature, 25°C (77°F).

Note: The storage conditions are based on stability studies of compounded oral suspensions, using the above mentioned vehicles, which were placed in glass and polyethyleneterephthalate (PET) bottles. Stability studies have not been conducted with other vehicles or bottle types.

Place a pharmacy label on the bottle that includes the patient's name, dosing instructions, and drug name and any other required information to be in compliance with all State and Federal Pharmacy Regulations.

Dosing of the Compounded Suspension (6 mg/mL)

Refer to Table 1 for the proper dosing instructions for the pharmacy label.

3 DOSAGE FORMS AND STRENGTHS

Capsules: 30 mg, 45 mg, 75 mg

- 30-mg capsules (30 mg free base equivalent of the phosphate salt): light yellow hard gelatin capsules. "ROCHE" is printed in blue ink on the light yellow body and "30 mg" is printed in blue ink on the light yellow cap.
- 45-mg capsules (45 mg free base equivalent of the phosphate salt): grey hard gelatin capsules. "ROCHE" is printed in blue ink on the grey body and "45 mg" is printed in blue ink on the grey cap.
- 75-mg capsules (75 mg free base equivalent of the phosphate salt): grey/light yellow hard gelatin capsules. "ROCHE" is printed in blue ink on the grey body and "75 mg" is printed in blue ink on the light yellow cap.

For Oral Suspension: 6 mg/mL (final concentration when constituted)

- White powder blend for constitution to a white tutti-frutti–flavored suspension. After constitution, each bottle delivers a usable volume of 60 mL of oral suspension equivalent to 360 mg oseltamivir base (6 mg/mL).

4 CONTRAINDICATIONS

TAMIFLU is contraindicated in patients with known serious hypersensitivity to oseltamivir or any component of the product. Severe allergic reactions have included anaphylaxis and serious skin reactions including toxic epidermal necrolysis, Stevens-Johnson Syndrome, and erythema multiforme [see Warnings and Precautions (5.1)].

5 WARNINGS AND PRECAUTIONS

5.1 Serious Skin/Hypersensitivity Reactions

Cases of anaphylaxis and serious skin reactions including toxic epidermal necrolysis, Stevens-Johnson Syndrome, and erythema multiforme have been reported in postmarketing experience with TAMIFLU. TAMIFLU should be stopped and appropriate treatment instituted if an allergic-like reaction occurs or is suspected.

5.2 Neuropsychiatric Events

Influenza can be associated with a variety of neurologic and behavioral symptoms that can include events such as hallucinations, delirium, and abnormal behavior, in some cases resulting in fatal outcomes. These events may occur in the setting of encephalitis or encephalopathy but can occur without obvious severe disease.

There have been postmarketing reports (mostly from Japan) of delirium and abnormal behavior leading to injury, and in some cases resulting in fatal outcomes, in patients with influenza who were receiving TAMIFLU. Because these events were reported voluntarily during clinical practice, estimates of frequency cannot be made but they appear to be uncommon based on TAMIFLU usage data. These events were reported primarily among pediatric patients and often had an abrupt onset and rapid resolution. The contribution of TAMIFLU to these events has not been established. Closely monitor patients with influenza for signs of abnormal behavior. If neuropsychiatric symptoms occur, evaluate the risks and benefits of continuing treatment for each patient.

5.3 Bacterial Infections

Serious bacterial infections may begin with influenza-like symptoms or may coexist with or occur as complications during the course of influenza. TAMIFLU has not been shown to prevent such complications.

5.4 Limitations of Populations Studied

Efficacy of TAMIFLU in the treatment of influenza in patients with chronic cardiac disease and/or respiratory disease has not been established. No difference in the incidence of complications was observed between the treatment and placebo groups in this population. No information is available regarding treatment of influenza in patients with any medical condition sufficiently severe or unstable to be considered at imminent risk of requiring hospitalization.

Efficacy of TAMIFLU for treatment or prophylaxis of influenza has not been established in immunocompromised patients.

6 ADVERSE REACTIONS

The following serious adverse reactions are discussed below and elsewhere in the labeling:

- Serious skin and hypersensitivity reactions [see Warnings and Precautions (5.1)]
- Neuropsychiatric events [see Warnings and Precautions (5.2)]

The most common adverse reactions are nausea and vomiting.

6.1 Clinical Trials Experience

Because clinical trials are conducted under widely varying conditions, adverse reaction rates observed in the clinical trials of a drug cannot be directly compared to rates in the clinical trials of another drug and may not reflect the rates observed in practice.

Treatment Studies in Adult Subjects

A total of 1171 subjects who participated in adult controlled clinical trials for the treatment of influenza were treated with TAMIFLU. The most frequently reported adverse events in these studies were nausea and vomiting. These events were generally of mild to moderate severity and usually occurred on the first 2 days of administration. Less than 1% of subjects discontinued prematurely from clinical trials due to nausea and vomiting.

Adverse events that occurred with an incidence of ≥1% in 1440 subjects taking placebo or TAMIFLU 75 mg twice daily in adult treatment studies are shown in Table 4. This summary includes 945 healthy young adults and 495 "at risk" subjects (elderly patients and patients with chronic cardiac or respiratory disease). Those events reported numerically more frequently in subjects taking TAMIFLU compared with placebo were nausea, vomiting, bronchitis, insomnia, and vertigo.

Prophylaxis Studies in Adult Subjects

A total of 4187 subjects (adolescents, healthy adults, and elderly) participated in prophylaxis studies, of whom 1790 received the recommended dose of 75 mg once daily for up to 6 weeks. Adverse events were qualitatively very similar to those seen in the treatment studies, despite a longer duration of dosing (see Table 4). Events reported more frequently in subjects receiving TAMIFLU compared to subjects receiving placebo in prophylaxis studies, and more commonly than in treatment studies, were aches and pains, rhinorrhea, dyspepsia and upper respiratory tract infections. However, the difference in incidence between TAMIFLU and placebo for these events was less than 1%. There were no clinically relevant differences in the safety profile of the 942 elderly subjects who received TAMIFLU or placebo, compared with the younger population.

Table 4 Most Frequent Adverse Events in Studies in Naturally Acquired Influenza in Subjects 13 Years of Age and Older
 | Treatment |  |  |  | Prophylaxis
Adverse Event [Adverse events included are all events reported in the treatment studies with frequency ≥1% in the TAMIFLU 75 mg twice daily group.] | Placebo N=716 |  | TAMIFLU 75 mg twice daily N=724 |  | Placebo/ No Prophylaxis [The majority of subjects received placebo; 254 subjects from a randomized, open-label postexposure prophylaxis study in households did not receive placebo or prophylaxis therapy.] N=1688 |  | TAMIFLU 75 mg once daily N=1790
Nausea (without vomiting) | 40 | (6%) | 72 | (10%) | 56 | (3%) | 129 | (7%)
Vomiting | 21 | (3%) | 68 | (9%) | 16 | (1%) | 39 | (2%)
Diarrhea | 70 | (10%) | 48 | (7%) | 40 | (2%) | 50 | (3%)
Bronchitis | 15 | (2%) | 17 | (2%) | 22 | (1%) | 15 | (1%)
Abdominal pain | 16 | (2%) | 16 | (2%) | 25 | (1%) | 37 | (2%)
Dizziness | 25 | (3%) | 15 | (2%) | 21 | (1%) | 24 | (1%)
Headache | 14 | (2%) | 13 | (2%) | 306 | (18%) | 326 | (18%)
Cough | 12 | (2%) | 9 | (1%) | 119 | (7%) | 94 | (5%)
Insomnia | 6 | (1%) | 8 | (1%) | 15 | (1%) | 22 | (1%)
Vertigo | 4 | (1%) | 7 | (1%) | 4 | (<1%) | 4 | (<1%)
Fatigue | 7 | (1%) | 7 | (1%) | 163 | (10%) | 139 | (8%)

Additional adverse events occurring in <1% of patients receiving TAMIFLU for treatment included unstable angina, anemia, pseudomembranous colitis, humerus fracture, pneumonia, pyrexia, and peritonsillar abscess.

Treatment Studies in Pediatric Subjects

A total of 1032 pediatric subjects aged 1 to 12 years (including 698 otherwise healthy pediatric subjects aged 1 to 12 years and 334 asthmatic pediatric subjects aged 6 to 12 years) participated in controlled clinical trials of TAMIFLU given for the treatment of influenza. A total of 515 pediatric subjects received treatment with TAMIFLU for oral suspension.

Adverse events occurring in ≥1% of pediatric subjects receiving TAMIFLU treatment are listed in Table 5. The most frequently reported adverse event was vomiting. Other events reported more frequently by pediatric subjects treated with TAMIFLU included abdominal pain, epistaxis, ear disorder, and conjunctivitis. These events generally occurred once and resolved despite continued dosing resulting in discontinuation of drug in 8 out of 515 (2%) cases.

The adverse event profile in adolescents is similar to that described for adult subjects and pediatric subjects aged 1 to 12 years.

Prophylaxis Studies in Pediatric Subjects

Pediatric subjects aged 1 to 12 years participated in a postexposure prophylaxis study in households, both as index cases (n=134) and as contacts (n=222). Gastrointestinal events were the most frequent, particularly vomiting. In a separate 6-week, uncontrolled, pediatric seasonal prophylaxis study (n=49), the adverse events noted were consistent with those previously observed (see Table 5).

Table 5 Most Frequent Adverse Events Occurring in Children Aged 1 to 12 Years in Studies in Naturally Acquired Influenza
 | Treatment Trials [Pooled data from trials of TAMIFLU treatment of naturally acquired influenza.] |  |  |  | Household Prophylaxis Trial [A randomized, open-label study of household transmission in which household contacts received either prophylaxis or no prophylaxis but treatment if they became ill. Only contacts who received prophylaxis or who remained on no prophylaxis are included in this table.]
Adverse Event [Adverse events included in Table 5 are all events reported in the treatment studies with frequency ≥1% in the TAMIFLU 75 mg twice daily group.] | Placebo N=517 |  | TAMIFLU 2 mg/kg twice daily N=515 |  | No Prophylaxis [Unit dose = age-based dosing of 30 mg, 45 mg, or 60 mg] N=87 |  | Prophylaxis with TAMIFLU once daily N=99
Vomiting | 48 | (9%) | 77 | (15%) | 2 | (2%) | 10 | (10%)
Diarrhea | 55 | (11%) | 49 | (10%) | - |  | 1 | (1%)
Otitis media | 58 | (11%) | 45 | (9%) | 2 | (2%) | 2 | (2%)
Abdominal pain | 20 | (4%) | 24 | (5%) | - |  | 3 | (3%)
Asthma (including aggravated) | 19 | (4%) | 18 | (3%) | 1 | (1%) | 1 | (1%)
Nausea | 22 | (4%) | 17 | (3%) | 1 | (1%) | 4 | (4%)
Epistaxis | 13 | (3%) | 16 | (3%) | - |  | 1 | (1%)
Pneumonia | 17 | (3%) | 10 | (2%) | 2 | (2%) | -
Ear disorder | 6 | (1%) | 9 | (2%) | - |  | -
Sinusitis | 13 | (3%) | 9 | (2%) | - |  | -
Bronchitis | 11 | (2%) | 8 | (2%) | 2 | (2%) | -
Conjunctivitis | 2 | (<1%) | 5 | (1%) | - |  | -
Dermatitis | 10 | (2%) | 5 | (1%) | - |  | -
Lymphadenopathy | 8 | (2%) | 5 | (1%) | - |  | -
Tympanic membrane disorder | 6 | (1%) | 5 | (1%) | - |  | -

Prophylaxis Study in Immunocompromised Subjects

In a 12-week seasonal prophylaxis study in 475 immunocompromised subjects, including 18 pediatric subjects 1 to 12 years of age, the safety profile in the 238 subjects receiving TAMIFLU was consistent with that previously observed in other TAMIFLU prophylaxis clinical trials.

6.2 Postmarketing Experience

The following adverse reactions have been identified during postapproval use of TAMIFLU. Because these reactions are reported voluntarily from a population of uncertain size, it is not possible to reliably estimate their frequency or establish a causal relationship to TAMIFLU exposure.

Body as a Whole: Swelling of the face or tongue, allergy, anaphylactic/anaphylactoid reactions, hypothermia

Dermatologic: Rash, dermatitis, urticaria, eczema, toxic epidermal necrolysis, Stevens-Johnson Syndrome, erythema multiforme [see Warnings and Precautions (5.1)]

Digestive: Hepatitis, liver function tests abnormal

Cardiac: Arrhythmia

Gastrointestinal disorders: Gastrointestinal bleeding, hemorrhagic colitis

Neurologic: Seizure

Metabolic: Aggravation of diabetes

Psychiatric: Abnormal behavior, delirium, including symptoms such as hallucinations, agitation, anxiety, altered level of consciousness, confusion, nightmares, delusions [see Warnings and Precautions (5.2)]

7 DRUG INTERACTIONS

Influenza Vaccines

The concurrent use of TAMIFLU with live attenuated influenza vaccine (LAIV) intranasal has not been evaluated. However, because of the potential for interference between these products, LAIV should not be administered within 2 weeks before or 48 hours after administration of TAMIFLU, unless medically indicated. The concern about possible interference arises from the potential for antiviral drugs to inhibit replication of live vaccine virus. Trivalent inactivated influenza vaccine can be administered at any time relative to use of TAMIFLU.

Overall Drug Interaction Profile for Oseltamivir

Information derived from pharmacology and pharmacokinetic studies of oseltamivir suggests that clinically significant drug interactions are unlikely.

Oseltamivir is extensively converted to oseltamivir carboxylate by esterases, located predominantly in the liver. Drug interactions involving competition for esterases have not been extensively reported in literature. Low protein binding of oseltamivir and oseltamivir carboxylate suggests that the probability of drug displacement interactions is low.

In vitro studies demonstrate that neither oseltamivir nor oseltamivir carboxylate is a good substrate for P450 mixed-function oxidases or for glucuronyl transferases.

Clinically important drug interactions involving competition for renal tubular secretion are unlikely due to the known safety margin for most of these drugs, the elimination characteristics of oseltamivir carboxylate (glomerular filtration and anionic tubular secretion) and the excretion capacity of these pathways. Coadministration of probenecid results in an approximate two-fold increase in exposure to oseltamivir carboxylate due to a decrease in active anionic tubular secretion in the kidney. However, due to the safety margin of oseltamivir carboxylate, no dose adjustments are required when coadministering with probenecid.

No pharmacokinetic interactions have been observed when coadministering oseltamivir with amoxicillin, acetaminophen, aspirin, cimetidine, antacids (magnesium and aluminum hydroxides and calcium carbonates), or warfarin.

8 USE IN SPECIFIC POPULATIONS

8.1 Pregnancy

TERATOGENIC EFFECTS

Pregnancy Category C

There are insufficient human data upon which to base an evaluation of risk of TAMIFLU to the pregnant woman or developing fetus. Studies for effects on embryo-fetal development were conducted in rats (50, 250, and 1500 mg/kg/day) and rabbits (50, 150, and 500 mg/kg/day) by the oral route. Relative exposures at these doses were, respectively, 2, 13, and 100 times human exposure in the rat and 4, 8, and 50 times human exposure in the rabbit. Pharmacokinetic studies indicated that fetal exposure was seen in both species. In the rat study, minimal maternal toxicity was reported in the 1500 mg/kg/day group. In the rabbit study, slight and marked maternal toxicities were observed, respectively, in the 150 and 500 mg/kg/day groups. There was a dose-dependent increase in the incidence rates of a variety of minor skeletal abnormalities and variants in the exposed offspring in these studies. However, the individual incidence rate of each skeletal abnormality or variant remained within the background rates of occurrence in the species studied.

Because animal reproductive studies may not be predictive of human response and there are no adequate and well-controlled studies in pregnant women, TAMIFLU should be used during pregnancy only if the potential benefit justifies the potential risk to the fetus.

8.3 Nursing Mothers

In lactating rats, oseltamivir and oseltamivir carboxylate are excreted in the milk. It is not known whether oseltamivir or oseltamivir carboxylate is excreted in human milk. TAMIFLU should, therefore, be used only if the potential benefit for the lactating mother justifies the potential risk to the breast-fed infant.

8.4 Pediatric Use

The safety and efficacy of TAMIFLU in pediatric patients younger than 1 year of age have not been studied. TAMIFLU is not indicated for either treatment or prophylaxis of influenza in pediatric patients younger than 1 year of age because of the unknown clinical significance of nonclinical animal toxicology data for human infants [see Nonclinical Toxicology (13.2)].

8.5 Geriatric Use

Of the total number of subjects in clinical studies of TAMIFLU for the treatment of influenza, 19% were 65 and over, while 7% were 75 and over. Of the total number of patients in clinical studies of TAMIFLU for the prophylaxis of influenza, 25% were 65 and over, while 18% were 75 and over. No overall differences in safety or effectiveness were observed between these subjects and younger subjects, and other reported clinical experience has not identified differences in responses between the elderly and younger subjects.

The safety of TAMIFLU in geriatric subjects has been established in clinical studies that enrolled 741 subjects (374 received placebo and 362 received TAMIFLU). Some seasonal variability was noted in the clinical efficacy outcomes [see Clinical Studies (14.1)].

Safety and efficacy have been demonstrated in elderly residents of nursing homes who took TAMIFLU for up to 42 days for the prevention of influenza. Many of these individuals had cardiac and/or respiratory disease, and most had received vaccine that season [see Clinical Studies (14.2)].

8.6 Renal Impairment

Dose adjustment is recommended for patients with a serum creatinine clearance between 10 and 30 mL/min [see Dosage and Administration (2.4) and Clinical Pharmacology (12.3)]. No recommended dosing regimens are available for patients with end-stage renal disease undergoing routine hemodialysis or continuous peritoneal dialysis treatment.

8.7 Hepatic Impairment

No dosage adjustment is required in patients with mild to moderate hepatic impairment. The safety and pharmacokinetics in patients with severe hepatic impairment have not been evaluated [see Dosage and Administration (2.5) and Clinical Pharmacology (12.3)].

10 OVERDOSAGE

At present, there has been no experience with overdose. Single doses of up to 1000 mg of TAMIFLU have been associated with nausea and/or vomiting.

11 DESCRIPTION

TAMIFLU (oseltamivir phosphate) is available as capsules containing 30 mg, 45 mg, or 75 mg oseltamivir for oral use, in the form of oseltamivir phosphate, and as a powder for oral suspension, which when constituted with water as directed contains 6 mg/mL oseltamivir base. In addition to the active ingredient, each capsule contains pregelatinized starch, talc, povidone K30, croscarmellose sodium, and sodium stearyl fumarate. The 30 mg capsule shell contains gelatin, titanium dioxide, yellow iron oxide, and red iron oxide. The 45 mg capsule shell contains gelatin, titanium dioxide, and black iron oxide. The 75 mg capsule shell contains gelatin, titanium dioxide, yellow iron oxide, black iron oxide, and red iron oxide. Each capsule is printed with blue ink, which includes FD&C Blue No. 2 as the colorant. In addition to the active ingredient, the powder for oral suspension contains sorbitol, monosodium citrate, xanthan gum, titanium dioxide, tutti-frutti flavoring, sodium benzoate, and saccharin sodium.

Oseltamivir phosphate is a white crystalline solid with the chemical name (3R,4R,5S)-4-acetylamino-5-amino-3(1-ethylpropoxy)-1-cyclohexene-1-carboxylic acid, ethyl ester, phosphate (1:1). The chemical formula is C16H28N2O4 (free base). The molecular weight is 312.4 for oseltamivir free base and 410.4 for oseltamivir phosphate salt. The structural formula is as follows:

12 CLINICAL PHARMACOLOGY

12.1 Mechanism of Action

Oseltamivir is an antiviral drug [see Clinical Pharmacology (12.4)].

12.3 Pharmacokinetics

Absorption and Bioavailability

Oseltamivir is readily absorbed from the gastrointestinal tract after oral administration of oseltamivir phosphate and is extensively converted predominantly by hepatic esterases to oseltamivir carboxylate. At least 75% of an oral dose reaches the systemic circulation as oseltamivir carboxylate. Exposure to oseltamivir is less than 5% of the total exposure after oral dosing (see Table 6).

Table 6 Mean (% CV) Pharmacokinetic Parameters of Oseltamivir and Oseltamivir Carboxylate Following Multiple Dosing of 75 mg Capsules Twice Daily (n=20)
Parameter | Oseltamivir | Oseltamivir Carboxylate
Cmax (ng/mL) | 65 (26) | 348 (18)
AUC0-12h (ng∙h/mL) | 112 (25) | 2719 (20)

Plasma concentrations of oseltamivir carboxylate are proportional to doses up to 500 mg given twice daily.

Coadministration with food has no significant effect on the peak plasma concentration (551 ng/mL under fasted conditions and 441 ng/mL under fed conditions) and the area under the plasma concentration time curve (6218 ng∙h/mL under fasted conditions and 6069 ng∙h/mL under fed conditions) of oseltamivir carboxylate.

Distribution

The volume of distribution (Vss) of oseltamivir carboxylate, following intravenous administration in 24 subjects, ranged between 23 and 26 liters.

The binding of oseltamivir carboxylate to human plasma protein is low (3%). The binding of oseltamivir to human plasma protein is 42%, which is insufficient to cause significant displacement-based drug interactions.

Metabolism

Oseltamivir is extensively converted to oseltamivir carboxylate by esterases located predominantly in the liver. Neither oseltamivir nor oseltamivir carboxylate is a substrate for, or inhibitor of, cytochrome P450 isoforms.

Elimination

Absorbed oseltamivir is primarily (>90%) eliminated by conversion to oseltamivir carboxylate. Plasma concentrations of oseltamivir declined with a half-life of 1 to 3 hours in most subjects after oral administration. Oseltamivir carboxylate is not further metabolized and is eliminated in the urine. Plasma concentrations of oseltamivir carboxylate declined with a half-life of 6 to 10 hours in most subjects after oral administration. Oseltamivir carboxylate is eliminated entirely (>99%) by renal excretion. Renal clearance (18.8 L/h) exceeds glomerular filtration rate (7.5 L/h), indicating that tubular secretion occurs in addition to glomerular filtration. Less than 20% of an oral radiolabeled dose is eliminated in feces.

Special Populations

Renal Impairment

Administration of 100 mg of oseltamivir phosphate twice daily for 5 days to patients with various degrees of renal impairment showed that exposure to oseltamivir carboxylate is inversely proportional to declining renal function. Oseltamivir carboxylate exposures in patients with normal and impaired renal function administered various dose regimens of oseltamivir are described in Table 7.

Table 7 Oseltamivir Carboxylate Exposures in Patients With Normal and Reduced Serum Creatinine Clearance
Parameter | Normal Renal Function |  |  | Impaired Renal Function
 | 75 mg once daily | 75 mg twice daily | 150 mg twice daily | Creatinine Clearance <10 mL/min |  | Creatinine Clearance >10 and <30 mL/min
 | 75 mg once daily | 75 mg twice daily | 150 mg twice daily | CAPD | Hemodialysis | 75 mg daily | 75 mg alternate days | 30 mg daily
 | 75 mg once daily | 75 mg twice daily | 150 mg twice daily | 30 mg weekly | 30 mg alternate HD cycle | 75 mg daily | 75 mg alternate days | 30 mg daily
Cmax | 259 [Observed values. All other values are predicted.] | 348 | 705 | 766 | 850 | 1638 | 1175 | 655
Cmin | 39 | 138 | 288 | 62 | 48 | 864 | 209 | 346
AUC48 [AUC normalized to 48 hours.] | 7476 | 10876 | 21864 | 17381 | 12429 | 62636 | 21999 | 25054

Hepatic Impairment

In clinical studies oseltamivir carboxylate exposure was not altered in patients with mild or moderate hepatic impairment [see Dosage and Administration (2.5) and Use in Specific Populations (8.7)].

Pediatric Patients

The pharmacokinetics of oseltamivir and oseltamivir carboxylate have been evaluated in a single-dose pharmacokinetic study in pediatric patients aged 5 to 16 years (n=18) and in a small number of pediatric patients aged 3 to 12 years (n=5) enrolled in a clinical trial. Younger pediatric patients cleared both the prodrug and the active metabolite faster than adult patients resulting in a lower exposure for a given mg/kg dose. For oseltamivir carboxylate, apparent total clearance decreases linearly with increasing age (up to 12 years). The pharmacokinetics of oseltamivir in pediatric patients over 12 years of age are similar to those in adult patients.

Geriatric Patients

Exposure to oseltamivir carboxylate at steady-state was 25% to 35% higher in geriatric patients (age range 65 to 78 years) compared to young adults given comparable doses of oseltamivir. Half-lives observed in the geriatric patients were similar to those seen in young adults. Based on drug exposure and tolerability, dose adjustments are not required for geriatric patients for either treatment or prophylaxis [see Dosage and Administration (2.6)].

12.4 Microbiology

Mechanism of Action

Oseltamivir phosphate is an ethyl ester prodrug requiring ester hydrolysis for conversion to the active form, oseltamivir carboxylate. Oseltamivir carboxylate is an inhibitor of influenza virus neuraminidase affecting release of viral particles.

Antiviral Activity

The antiviral activity and neuraminidase inhibitory activity of oseltamivir carboxylate against laboratory strains and clinical isolates of influenza virus was determined in cell culture and biochemical assays. The concentrations of oseltamivir carboxylate required for inhibition of influenza virus in cell culture were highly variable depending on the assay method used and the virus tested. The 50% and 90% effective concentrations (EC50 and EC90) were in the range of 0.0008 µM to >35 µM and 0.004 µM to >100 µM, respectively (1 µM=0.284 µg/mL). The median IC50 values of oseltamivir against influenza A/H1N1, influenza A/H3N2, and influenza B clinical isolates were 2.5 nM (range 0.93-4.16 nM, N=74), 0.96 nM (range 0.13-7.95 nM, N=774), and 60 nM (20-285 nM, N=256), respectively, in a neuraminidase assay with a fluorescently labeled MUNANA substrate. The relationship between the antiviral activity in cell culture, inhibitory activity in the neuraminidase assay, and the inhibition of influenza virus replication in humans has not been established.

Resistance

Influenza A virus isolates with reduced susceptibility to oseltamivir carboxylate have been recovered by serial passage of virus in cell culture in the presence of increasing concentrations of oseltamivir carboxylate, from clinical isolates collected during treatment with oseltamivir, and from viral isolates sampled during community surveillance studies. Reduced susceptibility of influenza virus to inhibition by oseltamivir carboxylate may be conferred by amino acid substitutions in the viral neuraminidase and/or hemagglutinin proteins. Changes in the viral neuraminidase that have been associated with reduced susceptibility to oseltamivir carboxylate are summarized in Table 8. Hemagglutinin substitutions associated with oseltamivir resistance include A28T and R124M in influenza A H3N2 and H154Q in H1N9, a reassortant human/avian virus.

Table 8 Neuraminidase Amino Acid Substitutions Observed in Oseltamivir Treatment Studies or Community Surveillance
Amino Acid Substitution | Influenza Type/ Sub-type | Source
Catalytic Residues
R292K | A N2 | Roche clinical trials, publication, surveillance [Substitutions identified by surveillance data only; population and use of TAMIFLU are unknown]
Framework Residues
H275Y | A N1 | Roche clinical trials, publication, surveillance
N294S | A N1, N2 | Publications
E119V | A N2 | Roche clinical trials, publication, surveillance
SASG245-248 deletion | A N2 | Roche clinical trial
I222V | A N2 | Publication
I222T | B | Publication
D198N | B | Publication, surveillance
D198E | B | Surveillance
R371K | B | Surveillance
G402S | B | Publication

Selection of influenza A viruses resistant to oseltamivir can occur at higher frequencies in children. The incidence of oseltamivir treatment-associated resistance in pediatric treatment studies has been detected at rates of 27% to 37% and 3% to 18% (3/11 to 7/19 and 1/34 to 9/50 post-treatment isolates, respectively) for influenza A/H1N1 and influenza A/H3N2, respectively. The frequency of resistance selection to oseltamivir and the prevalence of such resistant virus vary seasonally and geographically.

Circulating seasonal influenza strains expressing neuraminidase resistance-associated substitutions have been observed in individuals who have not received oseltamivir treatment. The oseltamivir resistance-associated substitution H275Y was found in >99% of US circulating 2008 H1N1 influenza isolates. The 2009 H1N1 influenza ("swine flu") was almost uniformly susceptible to oseltamivir. Prescribers should consider available information from the CDC on influenza drug susceptibility patterns and treatment effects when deciding whether to use TAMIFLU.

Cross-resistance

Cross-resistance between oseltamivir and zanamivir has been observed in neuraminidase biochemical assays. The H275Y (N1 numbering) or N294S (N2 numbering) oseltamivir resistance-associated substitutions observed in the N1 neuraminidase subtype, and the E119V or N294S oseltamivir resistance-associated substitutions observed in the N2 subtype (N2 numbering), are associated with reduced susceptibility to oseltamivir but not zanamivir. The Q136K and K150T zanamivir resistance-associated substitutions observed in N1 neuraminidase, or the S250G zanamivir resistance-associated substitutions observed in influenza B, confer reduced susceptibility to zanamivir but not oseltamivir. The R292K oseltamivir resistance-associated substitution observed in N2, and the I222T, D198E/N, R371K, or G402S oseltamivir resistance-associated substitutions observed in influenza B neuraminidase, confer reduced susceptibility to both oseltamivir and zanamivir. In general, amino acid substitutions at neuraminidase catalytic residues confer cross-resistance to other neuraminidase inhibitors while substitutions at framework residues may or may not confer cross-resistance.

No single amino acid substitution has been identified that could confer cross-resistance between the neuraminidase inhibitor class (oseltamivir, zanamivir) and the M2 ion channel inhibitor class (amantadine, rimantadine). However, a virus may carry a neuraminidase inhibitor associated substitution in neuraminidase and an M2 ion channel inhibitor associated substitution in M2 and may therefore be resistant to both classes of inhibitors. The clinical relevance of phenotypic cross-resistance evaluations has not been established.

Immune Response

No influenza vaccine/oseltamivir interaction study has been conducted. In studies of naturally acquired and experimental influenza, treatment with TAMIFLU did not impair normal humoral antibody response to infection.

13 NONCLINICAL TOXICOLOGY

13.1 Carcinogenesis, Mutagenesis, Impairment of Fertility

In 2-year carcinogenicity studies in mice and rats given daily oral doses of the prodrug oseltamivir phosphate up to 400 mg/kg and 500 mg/kg, respectively, the prodrug and the active form oseltamivir carboxylate induced no statistically significant increases in tumors over controls. The mean maximum daily exposures to the prodrug in mice and rats were approximately 130- and 320-fold, respectively, greater than those in humans at the proposed clinical dose based on AUC comparisons. The respective safety margins of the exposures to the active oseltamivir carboxylate were 15- and 50-fold.

Oseltamivir was found to be non-mutagenic in the Ames test and the human lymphocyte chromosome assay with and without enzymatic activation and negative in the mouse micronucleus test. It was found to be positive in a Syrian Hamster Embryo (SHE) cell transformation test. Oseltamivir carboxylate was non-mutagenic in the Ames test and the L5178Y mouse lymphoma assay with and without enzymatic activation and negative in the SHE cell transformation test.

In a fertility and early embryonic development study in rats, doses of oseltamivir at 50, 250, and 1500 mg/kg/day were administered to females for 2 weeks before mating, during mating and until day 6 of pregnancy. Males were dosed for 4 weeks before mating, during mating, and for 2 weeks after mating. There were no effects on fertility, mating performance or early embryonic development at any dose level. The highest dose was approximately 100 times the human systemic exposure (AUC0-24h) of oseltamivir carboxylate.

13.2 Animal Toxicology and/or Pharmacology

Single, oral administration of ≥657 mg/kg oseltamivir resulted in toxicity, including death, in juvenile 7 day old rats, but had no effect on adult rats. No toxicity was observed after repeated administration of up to 500 mg/kg oseltamivir to developing juvenile rats 7 to 21 days old. This 500 mg/kg dose was approximately 280 and 14 times the human systemic exposure (AUC0-24h) of oseltamivir and oseltamivir carboxylate, respectively. Clinical relevance of the juvenile rat study finding for young infants is unknown.

14 CLINICAL STUDIES

14.1 Treatment of Influenza

Adult Subjects

Two placebo-controlled double-blind clinical trials were conducted: one in the U.S. and one outside the U.S. Subjects were eligible for these trials if they had fever >100ºF, accompanied by at least one respiratory symptom (cough, nasal symptoms, or sore throat) and at least one systemic symptom (myalgia, chills/sweats, malaise, fatigue, or headache) and influenza virus was known to be circulating in the community. In addition, all subjects enrolled in the trials were allowed to take fever-reducing medications.

Of 1355 subjects enrolled in these two trials, 849 (63%) subjects were influenza-infected (age range 18 to 65 years; median age 34 years; 52% male; 90% Caucasian; 31% smokers). Of the 849 influenza-infected subjects, 95% were infected with influenza A, 3% with influenza B, and 2% with influenza of unknown type.

TAMIFLU was started within 40 hours of onset of symptoms. Subjects participating in the trials were required to self-assess the influenza-associated symptoms as "none," "mild," "moderate," or "severe." Time to improvement was calculated from the time of treatment initiation to the time when all symptoms (nasal congestion, sore throat, cough, aches, fatigue, headaches, and chills/sweats) were assessed as "none" or "mild." In both studies, at the recommended dose of TAMIFLU 75 mg twice daily for 5 days, there was a 1.3 day reduction in the median time to improvement in influenza-infected subjects receiving TAMIFLU compared to subjects receiving placebo. Subgroup analyses of these studies by gender showed no differences in the treatment effect of TAMIFLU in men and women.

In the treatment of influenza, no increased efficacy was demonstrated in subjects receiving treatment of 150 mg TAMIFLU twice daily for 5 days.

Geriatric Subjects

Three double-blind placebo-controlled treatment trials were conducted in subjects ≥65 years of age in three consecutive seasons. The enrollment criteria were similar to that of adult trials with the exception of fever being defined as >97.5°F. Of 741 subjects enrolled, 476 (65%) subjects were influenza-infected. Of the 476 influenza-infected subjects, 95% were infected with influenza type A and 5% with influenza type B.

In the pooled analysis, at the recommended dose of TAMIFLU 75 mg twice daily for 5 days, there was a 1-day reduction in the median time to improvement in influenza-infected subjects receiving TAMIFLU compared to those receiving placebo (p=NS). However, the magnitude of treatment effect varied between studies.

Pediatric Subjects

One double-blind placebo-controlled treatment trial was conducted in pediatric subjects aged 1 to 12 years (median age 5 years), who had fever (>100°F) plus one respiratory symptom (cough or coryza) when influenza virus was known to be circulating in the community. Of 698 subjects enrolled in this trial, 452 (65%) were influenza-infected (50% male; 68% Caucasian). Of the 452 influenza-infected subjects, 67% were infected with influenza A and 33% with influenza B.

The primary endpoint in this study was the time to freedom from illness, a composite endpoint that required 4 individual conditions to be met. These were: alleviation of cough, alleviation of coryza, resolution of fever, and parental opinion of a return to normal health and activity. TAMIFLU treatment of 2 mg/kg twice daily, started within 48 hours of onset of symptoms, significantly reduced the total composite time to freedom from illness by 1.5 days compared to placebo. Subgroup analyses of this study by gender showed no differences in the treatment effect of TAMIFLU in male and female pediatric subjects.

14.2 Prophylaxis of Influenza

Adult Subjects

The efficacy of TAMIFLU in preventing naturally occurring influenza illness has been demonstrated in three seasonal prophylaxis studies and a postexposure prophylaxis study in households. The primary efficacy parameter for all these studies was the incidence of laboratory-confirmed clinical influenza. Laboratory-confirmed clinical influenza was defined as oral temperature ≥99.0°F/37.2°C plus at least one respiratory symptom (cough, sore throat, nasal congestion) and at least one constitutional symptom (aches and pain, fatigue, headache, chills/sweats), all recorded within 24 hours, plus either a positive virus isolation or a four-fold increase in virus antibody titers from baseline.

In a pooled analysis of two seasonal prophylaxis studies in healthy unvaccinated adults (aged 13 to 65 years), TAMIFLU 75 mg once daily taken for 42 days during a community outbreak reduced the incidence of laboratory-confirmed clinical influenza from 5% (25/519) for the placebo group to 1% (6/520) for the TAMIFLU group.

In a seasonal prophylaxis study in elderly residents of skilled nursing homes, TAMIFLU 75 mg once daily taken for 42 days reduced the incidence of laboratory-confirmed clinical influenza from 4% (12/272) for the placebo group to <1% (1/276) for the TAMIFLU group. About 80% of this elderly population were vaccinated, 14% of subjects had chronic airway obstructive disorders, and 43% had cardiac disorders.

In a study of postexposure prophylaxis in household contacts (aged ≥13 years) of an index case, TAMIFLU 75 mg once daily administered within 2 days of onset of symptoms in the index case and continued for 7 days reduced the incidence of laboratory-confirmed clinical influenza from 12% (24/200) in the placebo group to 1% (2/205) for the TAMIFLU group. Index cases did not receive TAMIFLU in the study.

Pediatric Subjects

The efficacy of TAMIFLU in preventing naturally occurring influenza illness has been demonstrated in a randomized, open-label, postexposure prophylaxis study in households that included children aged 1 to 12 years, both as index cases and as family contacts. All index cases in this study received treatment. The primary efficacy parameter for this study was the incidence of laboratory-confirmed clinical influenza in the household. Laboratory-confirmed clinical influenza was defined as oral temperature ≥100°F/37.8°C plus cough and/or coryza recorded within 48 hours, plus either a positive virus isolation or a four-fold or greater increase in virus antibody titers from baseline or at illness visits. Among household contacts 1 to 12 years of age not already shedding virus at baseline, TAMIFLU for oral suspension 30 mg to 60 mg taken once daily for 10 days reduced the incidence of laboratory-confirmed clinical influenza from 17% (18/106) in the group not receiving prophylaxis to 3% (3/95) in the group receiving prophylaxis.

Immunocompromised Subjects

A double-blind, placebo-controlled study was conducted for seasonal prophylaxis of influenza in 475 immunocompromised subjects (including 18 pediatric subjects 1 to 12 years of age) who had received solid organ (n=388; liver, kidney, liver and kidney) or hematopoietic stem cell transplants (n=87). Median time since transplant for solid organ transplant recipients was 1105 days for the placebo group and 1379 days for the oseltamivir group. Median time since transplant for hematopoietic stem cell transplant recipients was 424 days for the placebo group and 367 days for the oseltamivir group. Approximately 40% of subjects received influenza vaccine prior to entering the study. The primary efficacy endpoint for this study was the incidence of confirmed, clinical influenza, defined as oral temperature >99.0°F/37.2°C plus cough and/or coryza, all recorded within 24 hours, plus either a positive virus culture or a four-fold increase in virus antibody titers from baseline. The incidence of confirmed clinical influenza was 3% (7/238) in the group not receiving TAMIFLU compared with 2% (5/237) in the group receiving TAMIFLU; this difference was not statistically significant. A secondary analysis was performed using the same clinical symptoms and RT-PCR for laboratory confirmation of influenza. Among subjects who were not already shedding virus at baseline, the incidence of RT-PCR-confirmed clinical influenza was 3% (7/231) in the group not receiving TAMIFLU and <1% (1/232) in the group receiving TAMIFLU.

16 HOW SUPPLIED/STORAGE AND HANDLING

TAMIFLU for Oral Suspension

Supplied as a white powder blend in a glass bottle. After constitution, the powder blend produces a white tutti-frutti–flavored oral suspension. After constitution with 55 mL of water, each bottle delivers a usable volume of 60 mL of oral suspension equivalent to 360 mg oseltamivir base (6 mg/mL). Each bottle is supplied with a bottle adapter and a 10 mL oral dispenser (NDC 42254-092-60).

Storage

Store dry powder at 25°C (77°F); excursions permitted to 15° to 30°C (59° to 86°F) [See USP Controlled Room Temperature].

Store constituted suspension under refrigeration for up to 17 days at 2° to 8°C (36° to 46°F). Do not freeze. Alternatively, store constituted suspension for up to 10 days at 25°C (77°F); excursions permitted to 15° to 30°C (59° to 86°F) [See USP Controlled Room Temperature].

17 PATIENT COUNSELING INFORMATION

See FDA-approved Patient Labeling (Patient Information)

17.1 Information for Patients

Patients and/or caregivers should be advised of the risk of severe allergic reactions (including anaphylaxis) or serious skin reactions and should stop TAMIFLU and seek immediate medical attention if an allergic-like reaction occurs or is suspected.

Patients and/or caregivers should be advised of the risk of neuropsychiatric events in patients with influenza and should contact their physician if they experience signs of abnormal behavior while receiving TAMIFLU. Their physician will determine if TAMIFLU treatment should be continued.

Instruct patients to begin treatment with TAMIFLU as soon as possible from the first appearance of flu symptoms. Similarly, prevention should begin as soon as possible after exposure, at the recommendation of a physician.

Instruct patients to take any missed doses as soon as they remember, except if it is near the next scheduled dose (within 2 hours), and then continue to take TAMIFLU at the usual times.

TAMIFLU is not a substitute for a flu vaccination. Patients should continue receiving an annual flu vaccination according to guidelines on immunization practices.

A bottle of TAMIFLU for oral suspension contains approximately 11 g sorbitol. One dose of 75 mg TAMIFLU for oral suspension delivers 2 g sorbitol. For patients with hereditary fructose intolerance, this is above the daily maximum limit of sorbitol and may cause dyspepsia and diarrhea.

Distributed by:

Genentech USA, Inc.
A Member of the Roche Group
1 DNA Way
South San Francisco, CA 94080-4990

Licensor:

Gilead Sciences, Inc.
Foster City, California 94404

TUCOS_640796_PI_2011_03(K)

© 2011 Genentech, Inc. All rights reserved.

Repackaged by:

Rebel Distributors Corp
Thousand Oaks, CA 91320

Patient Information
TAMIFLU®
(oseltamivir phosphate)

This leaflet contains important information about TAMIFLU (TAM-ih-flew). Read it well before you begin treatment. This information does not take the place of talking with your healthcare professional about your medical condition or your treatment. This leaflet does not list all the benefits and risks of TAMIFLU. If you have any questions about TAMIFLU, ask your healthcare professional. Only your healthcare professional can determine if TAMIFLU is right for you.

What is TAMIFLU?

TAMIFLU attacks the influenza virus and stops it from spreading inside your body. TAMIFLU treats flu at its source, by attacking the virus that causes the flu, rather than simply masking symptoms.

TAMIFLU is for treating adults and children age 1 and older with the flu whose flu symptoms started within the last day or two. TAMIFLU can also reduce the chance of getting the flu in people age 1 and older who have a higher chance of getting the flu because they spend time with someone who has the flu. TAMIFLU can also reduce the chance of getting the flu if there is a flu outbreak in the community.

What is "Flu"?

"The flu" is an infection caused by the influenza virus. Flu symptoms include fever (usually 100ºF to 103ºF in adults, and sometimes higher in children) and problems such as cough, sore throat, runny or stuffy nose, headaches, muscle aches, fever, and extreme tiredness. Many people use the term "flu" to mean any combination of these symptoms, such as the common cold, but true influenza infection is often worse and may last longer than a cold.

Flu outbreaks happen about once a year, usually in the winter, when the influenza virus spreads widely in the community. Outside of those outbreaks, only a very tiny number of respiratory infections are caused by the influenza virus.

Should I get a flu shot?

TAMIFLU is not a substitute for a flu vaccination. You should continue to get a flu vaccination every year, according to your healthcare professional's advice.

Who should not take TAMIFLU?

Do not take TAMIFLU if you are allergic to the main ingredient, oseltamivir phosphate, or to any other ingredients of TAMIFLU. Before starting treatment, make sure your healthcare professional knows if you take any other medicines, or are pregnant, planning to become pregnant, or breastfeeding. TAMIFLU is normally not recommended for use during pregnancy or nursing, as the effects on the unborn child or nursing infant are unknown. TAMIFLU is not recommended for use in children younger than 1 year of age.

Tell your healthcare professional if you have any type of kidney disease, heart disease, respiratory disease, or any serious health condition.

TAMIFLU for Oral Suspension contains sorbitol. Sorbitol may cause upset stomach and diarrhea in patients with a family history of fructose intolerance.

How should I take TAMIFLU?

It is important that you begin your treatment with TAMIFLU as soon as possible from the first appearance of your flu symptoms or soon after you are exposed to the flu. If you feel worse or develop new symptoms during treatment with TAMIFLU, or if your flu symptoms do not start to get better, you should contact your healthcare professional.

If you have the flu: Take TAMIFLU twice a day for 5 days, once in the morning and once in the evening. You should complete the entire treatment of 10 doses (capsules or suspension), even if you feel better.

To prevent the flu: If someone in your home has the flu, take TAMIFLU once a day for 10 days or for as long as prescribed. You can take TAMIFLU for up to 6 weeks if you are exposed to the flu because of an outbreak in your community. Follow your healthcare professional's advice on how long to take TAMIFLU.

You can take TAMIFLU with food or without food. There is less chance of stomach upset if you take it with a light snack, milk, or a meal.

If you are taking TAMIFLU for Oral Suspension, your pharmacist will give you a dosing dispenser to measure the proper amount of Oral Suspension for your dose. Follow your healthcare professional's instructions on how to measure the proper dose for you. Review the instructions below on how to use the dispenser and ask your pharmacist if you have any questions. If you lose or damage the dispenser and cannot use it, contact your healthcare professional or pharmacist for advice on the proper dose.

If TAMIFLU for Oral Suspension is not available, your healthcare provider may instruct you to open TAMIFLU Capsules and mix the contents with sweetened liquids such as regular or sugar-free chocolate syrup, corn syrup, caramel topping, or light brown sugar (dissolved in water). Please follow the dosing instructions below.

If you forget to take your medicine, take the missed dose as soon as you remember, except if it is 2 hours or less before your next dose. Then continue to take TAMIFLU at the usual times. Do not take 2 doses at a time to make up for a missed dose. If you miss several doses, tell your healthcare professional and follow the advice given to you.

What are the possible side effects of TAMIFLU?

The most common side effects of TAMIFLU are nausea and vomiting. These are usually mild to moderate. They usually happen in the first 2 days of treatment. Taking TAMIFLU with food may reduce the chance of getting these side effects.

If you develop an allergic reaction or severe rash, stop taking TAMIFLU and contact your healthcare professional.

People with the flu, particularly children and adolescents, may be at an increased risk of seizures, confusion, or abnormal behavior early during their illness. These events may occur shortly after beginning TAMIFLU or may occur when flu is not treated. These events are uncommon but may result in accidental injury to the patient. Therefore, patients should be observed for signs of unusual behavior and a healthcare professional should be contacted immediately if the patient shows any signs of unusual behavior.

Before taking TAMIFLU, please let your healthcare provider know if you have received nasally administered influenza virus vaccine during the past two weeks.

If you notice any side effects not mentioned in this leaflet, or if you have any concerns about the side effects you get, tell your healthcare professional.

How and where should I store TAMIFLU?

TAMIFLU Capsules should be stored at room temperature, 77°F (25°C) and kept in a dry place. Keep this medication out of reach of children.

TAMIFLU for Oral Suspension should be stored under refrigeration for up to 17 days at 36° to 46°F (2° to 8°C). Do not freeze. Alternatively, store at room temperature for up to 10 days. Discard any unused portion when you are finished with your prescribed dosing of TAMIFLU.

General advice about prescription medicines:

Medicines are sometimes prescribed for conditions that are not mentioned in patient information leaflets. Do not use TAMIFLU for a condition for which it was not prescribed. Do not give TAMIFLU to other people, even if they have the same symptoms you have. It may not be right for them.

This leaflet summarizes the most important information about TAMIFLU. If you would like more information, talk with your healthcare professional. You can ask your pharmacist or healthcare professional for information about TAMIFLU that is written for health professionals.

DOSING INSTRUCTIONS FOR PATIENTS:

How Do I Prepare a Dose of TAMIFLU for Oral Suspension?

Please follow instructions carefully to ensure proper dosing of the oral suspension.

- Shake closed bottle well for about 5 seconds before each use.
- Remove child-resistant cap.
- Before inserting the tip of the oral dispenser into bottle adapter, push the plunger completely down toward the tip of the oral dispenser. Insert tip firmly into opening of the bottle adapter.
- Turn the entire unit (bottle and oral dispenser) upside down.
- Pull the plunger out slowly until the desired amount of medication is withdrawn into the oral dispenser (see figure). The 12.5 mL (75 mg) dose is obtained by filling the dispenser twice, once to the 10 mL graduation, and a second fill to the 2.5 mL graduation.

- Turn the entire unit right side up and remove the oral dispenser slowly from the bottle.
- Dispense directly into mouth. Do not mix with any liquid prior to dispensing.
- Close bottle with child-resistant cap after each use.
- Disassemble oral dispenser, rinse under running tap water and air dry prior to next use.

If Directed by My Healthcare Provider, How Do I Mix the Contents of TAMIFLU Capsules with Sweetened Liquids?

Please follow instructions carefully to ensure proper dosing.

- Holding one capsule over a small bowl, carefully pull the capsule open and pour the complete contents of the capsule into the bowl.
- Add to the capsule contents a small amount of a sweetened liquid such as chocolate syrup (regular or sugar-free), corn syrup, caramel topping, or light brown sugar (dissolved in water) that the child will consume completely.
- Stir the mixture and give the entire dose to the child.

Distributed by:

Genentech USA, Inc.
A Member of the Roche Group
1 DNA Way
South San Francisco, CA 94080-4990

Licensor:

Gilead Sciences, Inc.
Foster City, California 94404

TUCOS_640796_PPI_2011_03(K)

Rev. March 2011

© 2011 Genentech, Inc. All rights reserved.

Repackaged by:

Rebel Distributors Corp
Thousand Oaks, CA 91320

PACKAGE LABEL

PRINCIPAL DISPLAY PANEL